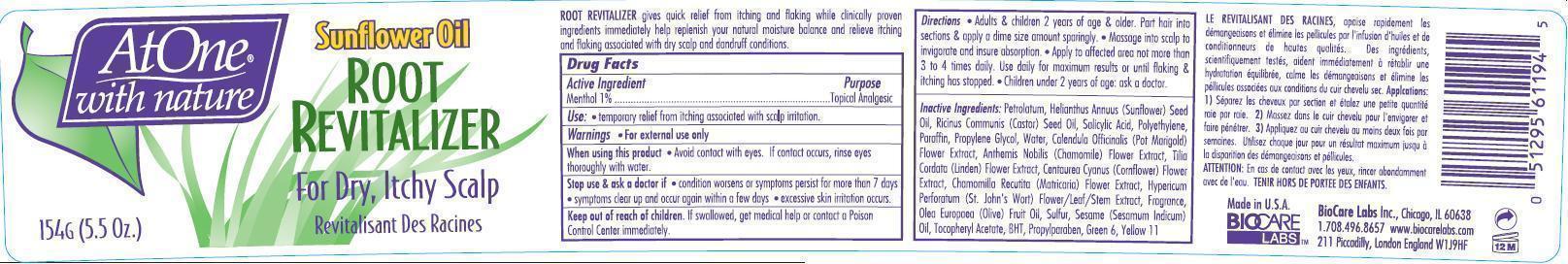 DRUG LABEL: At One With Nature
NDC: 54602-011 | Form: GEL, DENTIFRICE
Manufacturer: BIOCARE LABS INC.
Category: otc | Type: HUMAN OTC DRUG LABEL
Date: 20141103

ACTIVE INGREDIENTS: Menthol 10 mg/1 g
INACTIVE INGREDIENTS: PETROLATUM; SUNFLOWER OIL; CASTOR OIL; SALICYLIC ACID; HIGH DENSITY POLYETHYLENE; PARAFFIN; PROPYLENE GLYCOL; WATER; CALENDULA OFFICINALIS FLOWER; CHAMAEMELUM NOBILE FLOWER; TILIA CORDATA FLOWER; CENTAUREA CYANUS FLOWER; CHAMOMILE; HYPERICUM PERFORATUM; OLIVE OIL; SULFUR; SESAME OIL; .ALPHA.-TOCOPHEROL ACETATE; BUTYLATED HYDROXYTOLUENE; PROPYLPARABEN; D&C GREEN NO. 6; D&C YELLOW NO. 11

At One with nature Root Revitalizer for Dry Itchy Scalp

ACTIVE INGREDIENT

Menthol 1.00%

PURPOSE

Topical Analgesic

USE

temporary relief of itching associated with scalp irritation.

WARNINGS

- for external use only

When using this product

- avoid contact with eyes. If contact occurs rinse eyes thoroughly with water.

Stop use and ask a doctor if

- condition worsens, or if symptoms persist for more than 7 days
- symptoms clear up and occur again within a few days.
- excessive skin irritation

Keep out of reach of children.

If swallowed, get medical help or contact a Poison Control Center immediately.

Directions

- Adult & children 2 year of age & older. Part hair into section & apply a dime size amount sparingly.
- Massage into scalp to invigorate and insure absorption.
- Apply to affected area not more then 3 to 4 times daily. Use daily for maximum results or flaking & itching has stopped.
- Children under 2 years of age ask a doctor

INACTIVE INGREDIENTS

Petrolatum, Helianthus Annuus (Sunflower) Seed Oil, Ricinus Communis (Castor) Seed Oil, Salicylic Acid, Polyethylene, Paraffin, Propylene Glycol, Water, Calendula Officinalis (Pot Marigold) Flower Extract, Anthemis Nobilis Chamomile Flower Extract , Tilia Cordata (Linden)Flower Extract, Centaurea Cyanus (Cornflower) Flower Extract, Chamomilla Recutita (Matricaria) Flower Extract, Hypericum Perforatum Extract (St. John's Wort) Extract, Fragrance, Olea Europaea (Olive) Fruit Oil, Sulfur, Sesame (Sesamum Indicum) Oil, Tocopheryl Acetate, BHT, Propylparaben, Green 6, Yellow 11

PRINCIPAL DISPLAY PANEL

biocare5oz